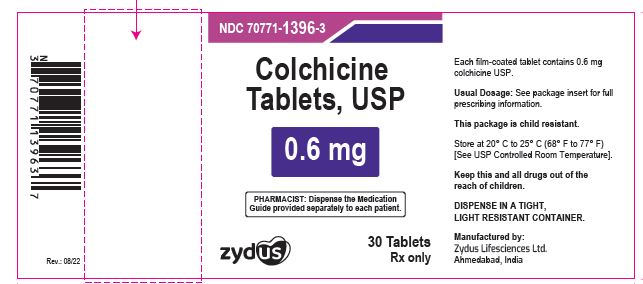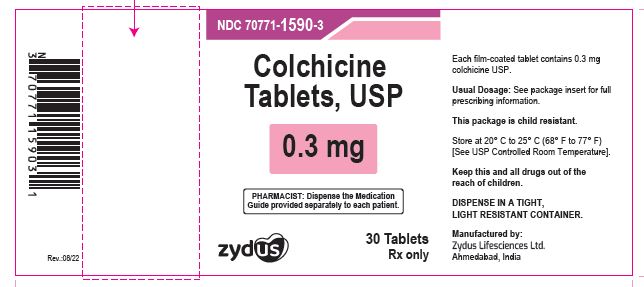 DRUG LABEL: Colchicine
NDC: 70771-1396 | Form: TABLET
Manufacturer: Zydus Lifesciences Limited
Category: prescription | Type: HUMAN PRESCRIPTION DRUG LABEL
Date: 20241126

ACTIVE INGREDIENTS: COLCHICEINE 0.6 mg/1 1
INACTIVE INGREDIENTS: CARMINIC ACID; FD&C BLUE NO. 2; FERROSOFERRIC OXIDE; HYDROXYPROPYL CELLULOSE, UNSPECIFIED; HYPROMELLOSE 2910 (5 MPA.S); HYPROMELLOSE 2910 (6 MPA.S); LACTOSE MONOHYDRATE; MAGNESIUM STEARATE; MICROCRYSTALLINE CELLULOSE; SODIUM STARCH GLYCOLATE TYPE A POTATO; STARCH, CORN; TALC; TITANIUM DIOXIDE

COLCHICINE TABLETS

PACKAGE LABEL.PRINCIPAL DISPLAY PANEL

NDC 70771-1396-3

Colchicine tablets, USP 0.6 mg

30 Tablets

Rx only

NDC 70771-1590-3

Colchicine tablets, USP 0.3 mg

30 Tablets

Rx only